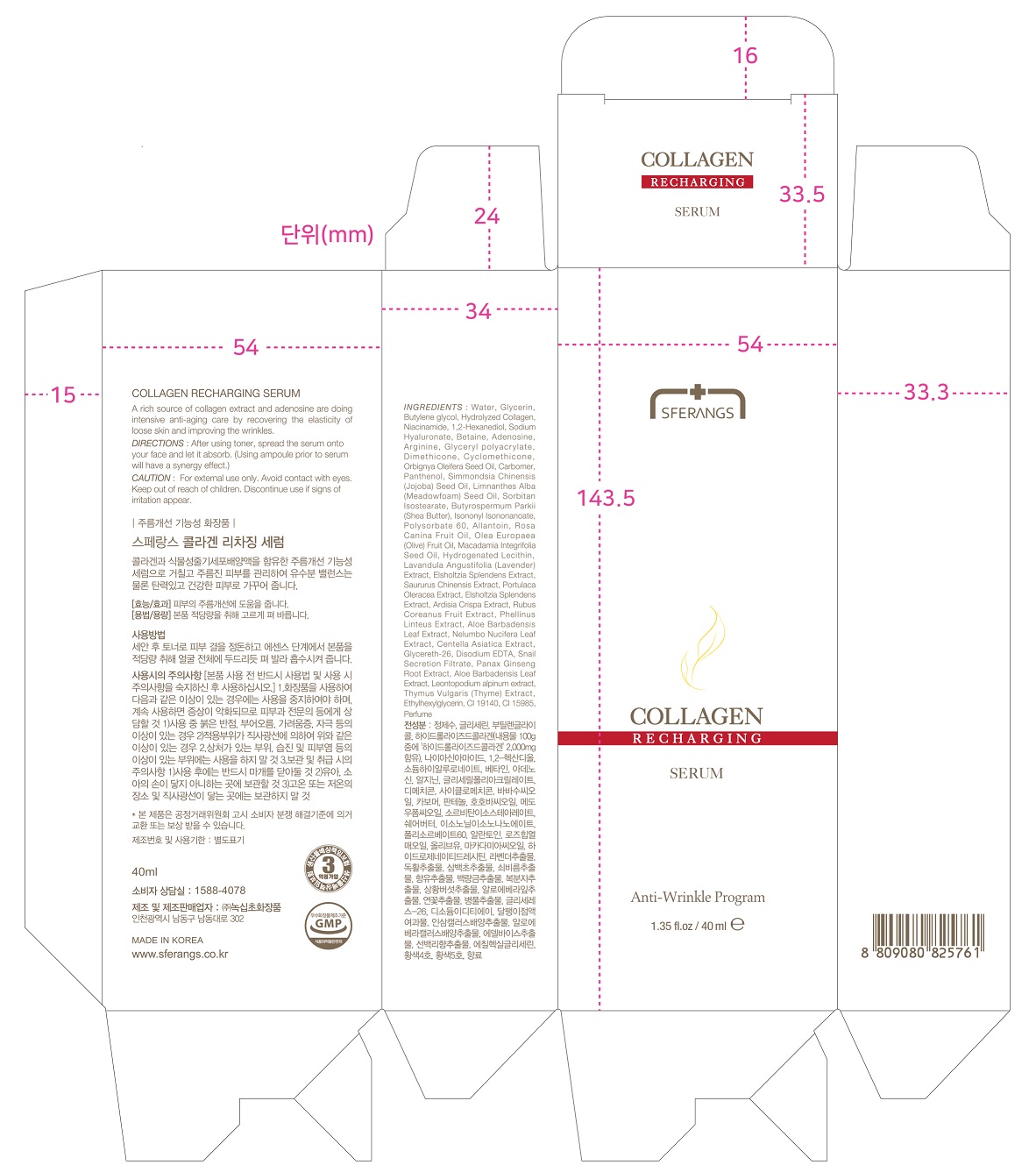 DRUG LABEL: SFERANGS COLLAGEN RECHARGING SERUM
NDC: 73590-0037 | Form: LIQUID
Manufacturer: NOKSIBCHO cosmetic Co., Ltd.
Category: otc | Type: HUMAN OTC DRUG LABEL
Date: 20200430

ACTIVE INGREDIENTS: ADENOSINE 0.04 g/100 mL
INACTIVE INGREDIENTS: WATER

Drug Facts

ACTIVE INGREDIENT

adenosine

INACTIVE INGREDIENT

Water
Glycerin
Butylene glycol
Hydrolyzed Collagen
1,2-Hexanediol
Niacinamide
Sodium Hyaluronate
Phenoxyethanol
Betaine
Arginine
Glyceryl polyacrylate
Orbignya Oleifera Seed Oil
Carbomer
Panthenol
Simmondsia Chinensis (Jojoba) Seed Oil
Limnanthes Alba (Meadowfoam) Seed Oil
Sorbitan Isostearate
Butyrospermum Parkii (Shea Butter)
Isononyl Isononanoate
Polysorbate 60
Allantoin
Rosa Canina Fruit Oil
Olea Europaea (Olive) Fruit Oil
Macadamia Integrifolia Seed Oil
Dimethicone
Hydrogenated Lecithin
Lavandula Angustifolia (Lavender) Extract
Propylene Glycol
Solanum Lycopersicum (Tomato) Fruit Extract
Paeonia Lactiflora Extract
Lonicera Japonica (Honeysuckle) Flower Extract
Phellinus Linteus Extract
Aloe Barbadensis Leaf Extract
Nelumbo Nucifera Leaf Extract
Centella Asiatica Extract
Glycereth-26
Disodium EDTA
Snail Secretion Filtrate
Panax ginseng culture extract
Caprylyl Glycol
Aloe vera Callus Culture Extract
Tropolone
Leontopodium alpinum extract
Thymus Vulgaris (Thyme) Extract
Ethylhexylglycerin
CI 19140
CI 15985
Parfum

PURPOSE

anti-wrinkle

keep out of reach of the children

INDICATIONS AND USAGE

apply proper amount to the skin

WARNINGS

For external use only
When using this product

■ if the following symptoms occurs after use, stop use and consult with a skin specialist

red specks, swelling, itching

■ don’t use on the part where there is injury, eczema, or dermatitis

Keep out of reach of children

■ if swallowed, get medical help or contact a person control center immediately